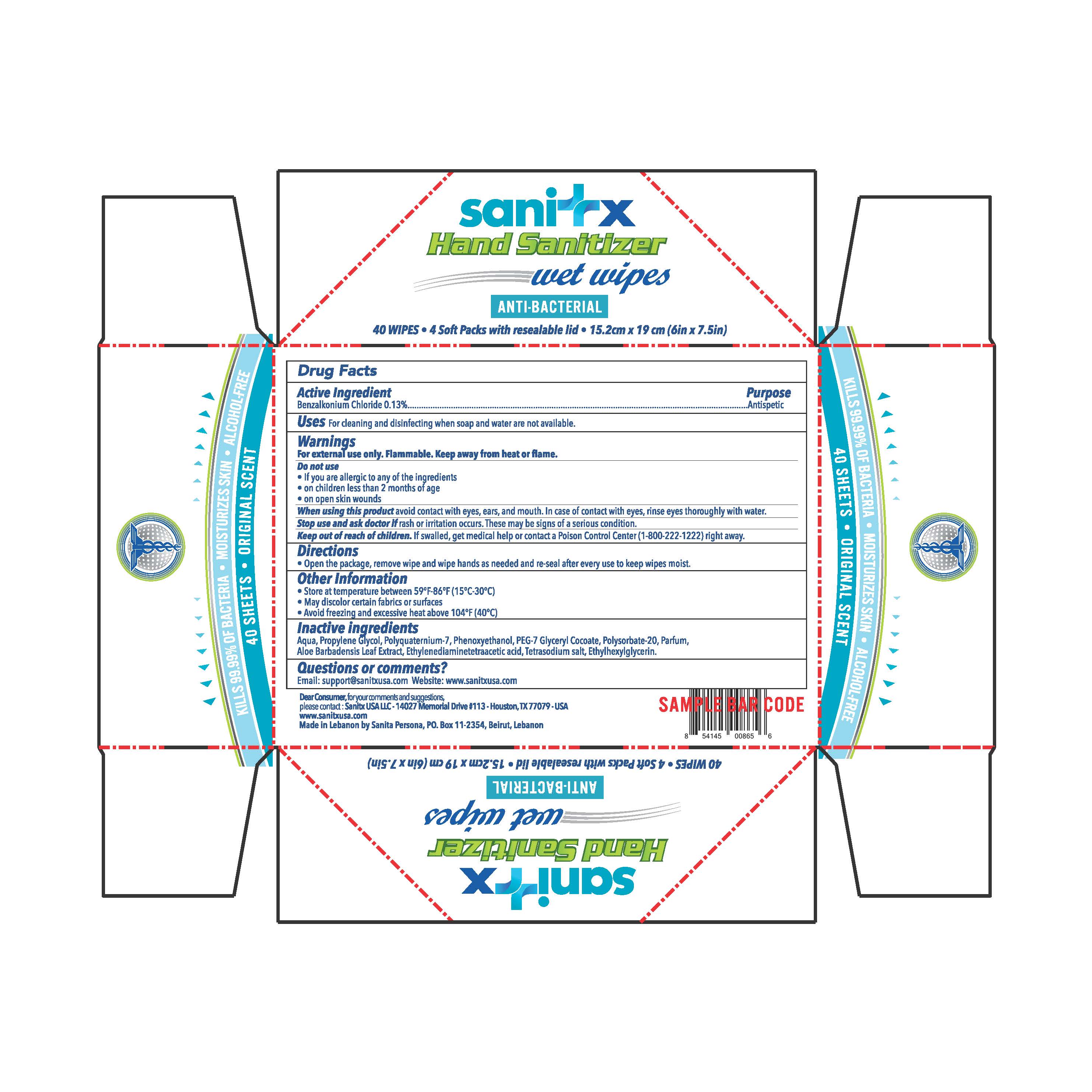 DRUG LABEL: Sanitx Wet Wipes
NDC: 78822-100 | Form: LIQUID
Manufacturer: SANITA PERSONA SAL
Category: otc | Type: HUMAN OTC DRUG LABEL
Date: 20200717

ACTIVE INGREDIENTS: BENZALKONIUM CHLORIDE 0.00013 1/1 1
INACTIVE INGREDIENTS: PEG-7 GLYCERYL COCOATE; POLYSORBATE 20; ETHYLHEXYLGLYCERIN; UREA; PHENOXYETHANOL; SOLASULFONE; METHYLISOTHIAZOLINONE; ALOE VERA LEAF; EDETIC ACID; PROPYLENE GLYCOL; WATER

Sanitx Wet Wipes

Active ingedient

Benzalkonium Chloride 0.13%

Purpose

Antimicrobial

Uses

Hand sanitizer to help reduce bacteria on the skin

Warnings

For external use only

Do not use if you are allergic to any of the ingredients

When using this product avoid contact with eyes. If contact occurs, rinse eyes thoroughly with water. avoid contact with broken, irritated, or itching skin.

Stop use and ask a doctor if irritation or redness develops and the condition persists for more than 72 hours.

Keep out of reach of children

If swallowed, get medical help or contact a Poison Control Center (1-800-222-1222) right away.

Directions

- Wet hands thoroughly with product and allow to dry
- Discard wipe in a trash receptacle after use. Do not flush.
- Children under 6 years of age should be supervised.

Inactive ingredients

Aqua, Propylene glycol, Polyquaternium-7, Phenoxyethanol, PEG-7 Glyceryl Cocoate, Polysorbate-20, Parfum, Aloe Barbadensis Leaf Extract, Urea, Ethylenediaminetetraacetic acid, Tetrasodium salt, Ethylhexylglycerin, Methylisothiazolinone